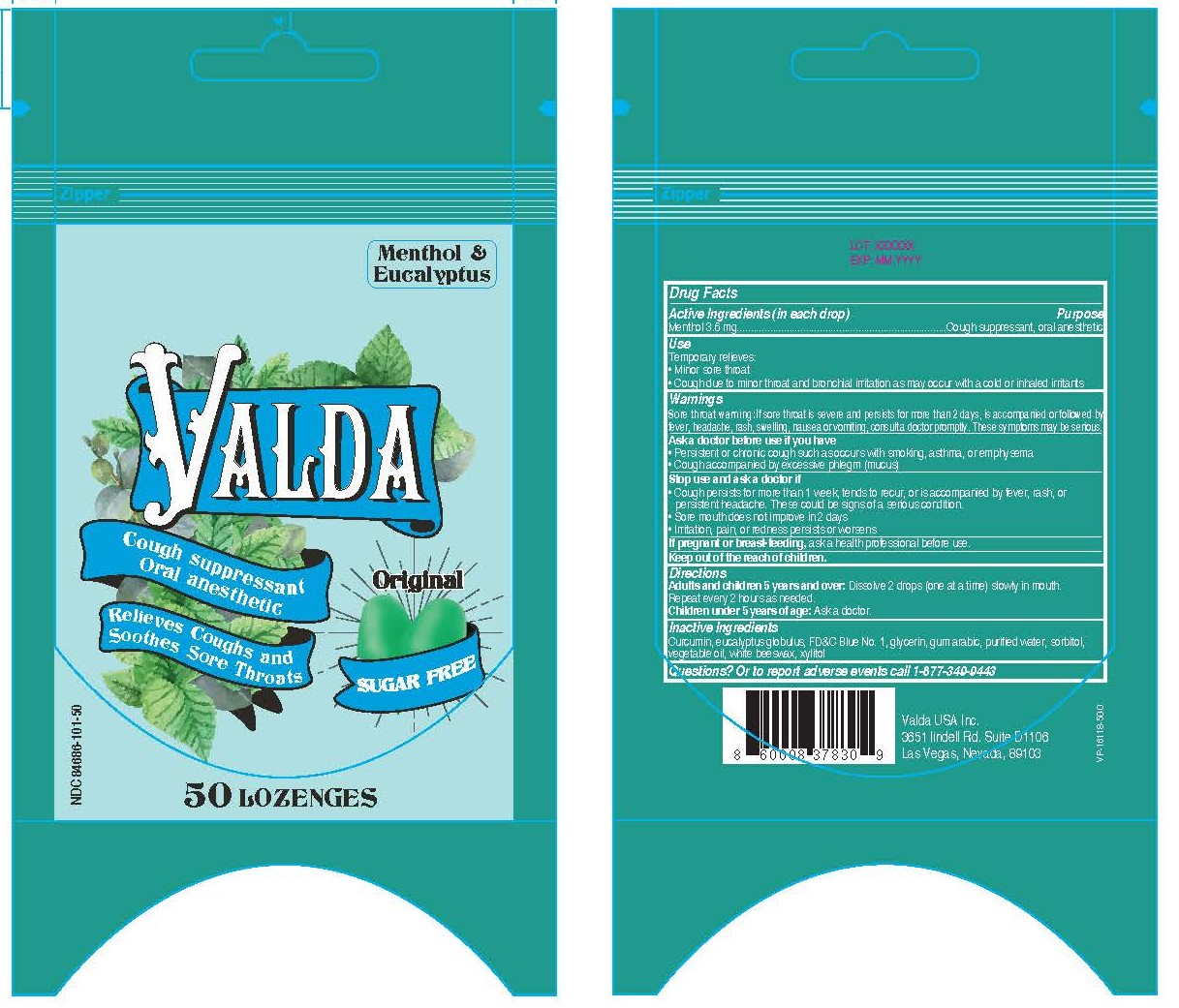 DRUG LABEL: ORIGINAL MENTHOL AND EUCALYPTUS SUGAR FREE
NDC: 84686-101 | Form: LOZENGE
Manufacturer: Valda USA Labeler
Category: otc | Type: HUMAN OTC DRUG LABEL
Date: 20241220

ACTIVE INGREDIENTS: MENTHOL 3.6 mg/1 1
INACTIVE INGREDIENTS: CURCUMIN; EUCALYPTUS GLOBULUS WHOLE; FD&C BLUE NO. 1; GLYCERIN; ACACIA; WATER; SORBITOL; CORN OIL; BEESWAX; XYLITOL

ORIGINAL MENTHOL AND EUCALYPTUS SUGAR FREE

Drug Facts

Purpose

Cough suppressant, oral anesthetic

Active Ingredient (in each drop)

Menthol, 3.6 mg

Uses

Temporarily relieves:

- Minor sore throat
- Cough due to minor throat and bronchial irritation as may occur with a cold or inhaled irritants

Warnings

Sore throat warning: If sore throat is severe and persists for more than 2 days, is accompanied or followed by fever, headache, rash, swelling, nausea, or vomiting, consult a doctor promptly. These symptoms may be serious.

Ask doctor before use if you have

- Persistent chronic cough such as occurs with smoking, asthma, or emphysema
- Cough accompanied by excessive phlegm (mucus)

Stop use and ask a doctor if

- Cough persists for more than 1 week, tends to recur, or is accompanied by fever, rash, or persistent headache. These could be signs of a serious condition.
- Sore mouth does not improve in 2 days
- Irritation, pain, or redness persists or worsens

Directions

- Adults and children 5 years and over: Dissolve 2 drops (one at a time) slowly in mouth. Repeat every 2 hours as needed.
- Children under 5 years of age: Ask a doctor.

Inactive Ingredients

Curcumin, eucalyptus globulus, FD&C Blue No. 1, glycerin, gum arabic, purified water, sorbitol, vegetable oil, white beeswax, xylitol

Questions?

Or to report adverse events call 1-877-349-9443